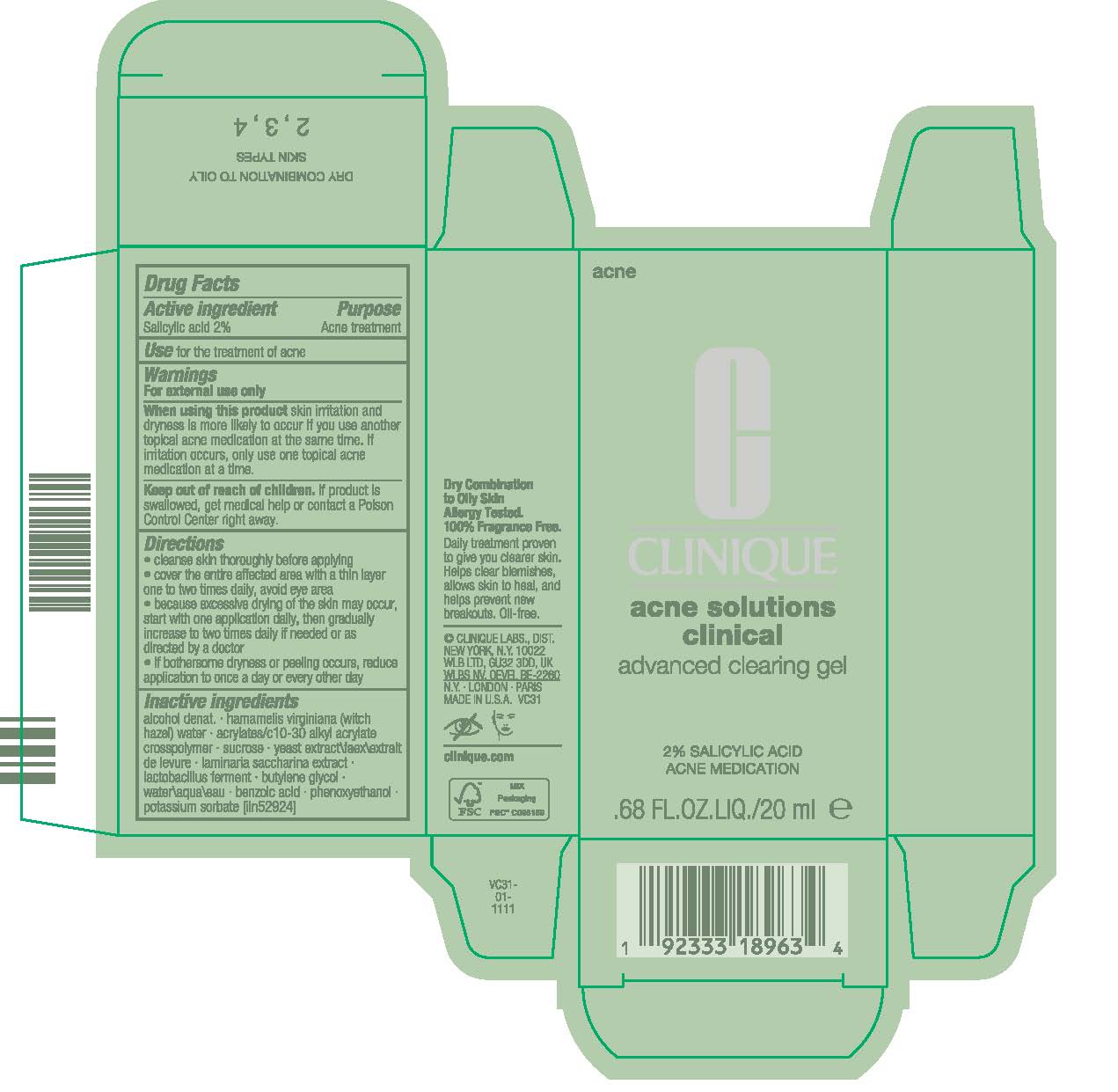 DRUG LABEL: ACNE SolutionS CLINICAL ADVANCED CLEARING gel
NDC: 49527-221 | Form: GEL
Manufacturer: CLINIQUE LABORATORIES LLC
Category: otc | Type: HUMAN OTC DRUG LABEL
Date: 20250303

ACTIVE INGREDIENTS: SALICYLIC ACID 20 mg/1 mL
INACTIVE INGREDIENTS: SUCROSE; BENZOIC ACID; SACCHARINA LATISSIMA; YEAST; PHENOXYETHANOL; DEHYDRATED ALCOHOL; HAMAMELIS VIRGINIANA TOP WATER; ACRYLATES/C10-30 ALKYL ACRYLATE CROSSPOLYMER (60000 MPA.S); BUTYLENE GLYCOL; WATER; POTASSIUM SORBATE

ACNE SOLUTIONS CLINICAL ADVANCED CLEARING GEL

Active ingredient

Salicylic acid 2%

Purpose

Acne Treatment

Use

for the treatment of acne

Warnings

For external use only

When using this product

skin irritation and dryness is more likely to occur if you use another topical acne medication at the same time. If irritation occurs, only use one topical acne medication at a time

Keep out of reach of children

If swallowed, get medical help or contact a Poison Control Center right away

Directions

- cleanse skin thoroughly before applying
- cover the entire affected area with a thin layer one to two times daily, avoid eye area
- because excessive drying of the skin may occur, start with one application daily, then gradually increase to two times daily if needed or as directed by a doctor
- if bothersome dryness or peeling occurs, reduce application to once a day or every other day

Inactive Ingredients

alcohol denat.,hamamelis virginiana (witch hazel) water,acrylates/c10-30 alkyl acrylate crosspolymer,sucrose,yeast extract\faex\extrait de levure,laminaria saccharina extract,lactobacillus ferment,butylene glycol,water\aqua\eau,benzoic acid,phenoxyethanol,potassium sorbate <iln52924>

PACKAGE LABEL

CLINIQUE
acne solutions
clinical

advanced clearing gel

2% SALICYLIC ACID
ACNE MEDICATION

0.68 FL.OZ.LIQ/20 ml